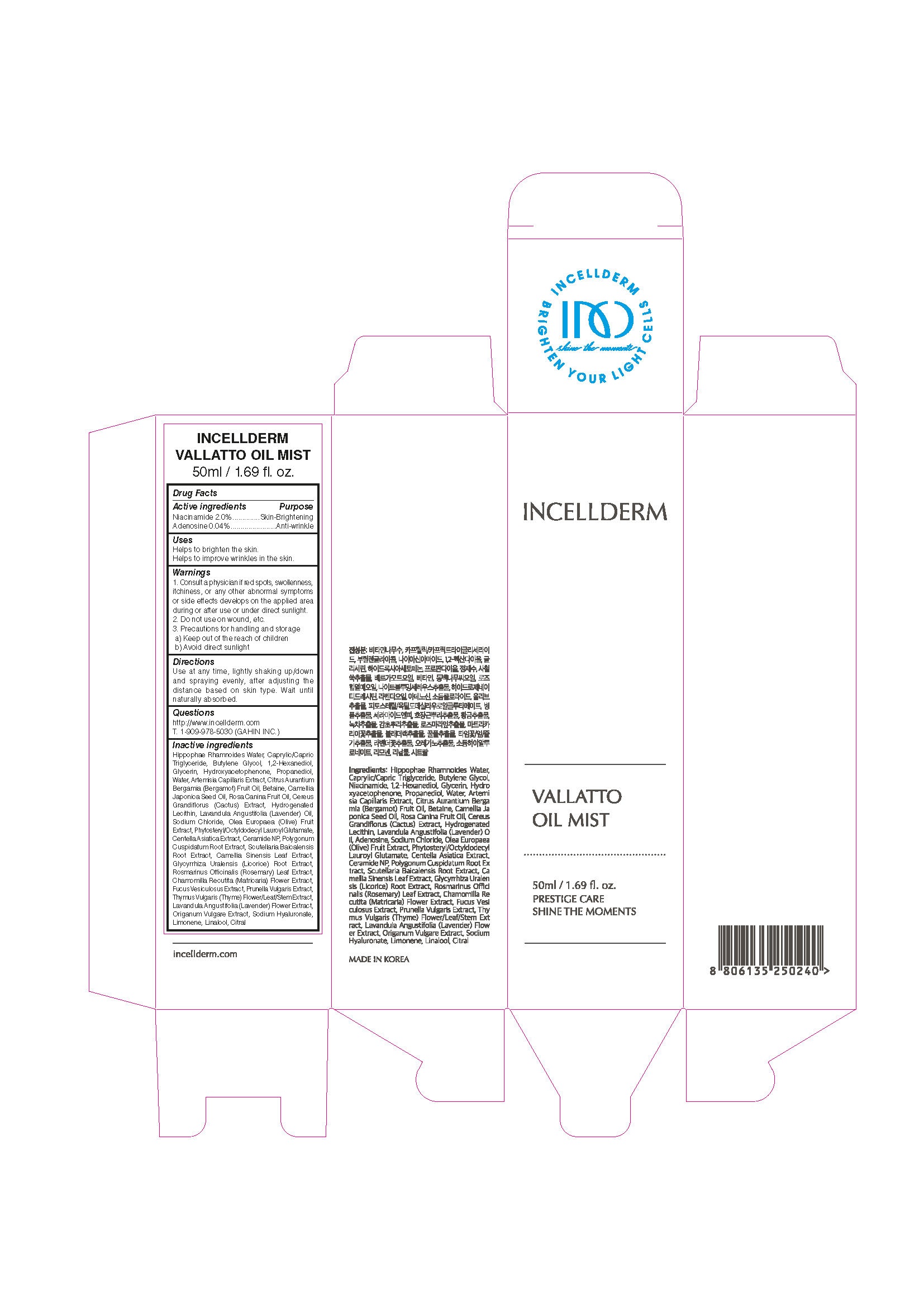 DRUG LABEL: INCELLDERM VIETON OILMIST
NDC: 72650-105 | Form: OIL
Manufacturer: Riman Korea Co., Ltd.
Category: otc | Type: HUMAN OTC DRUG LABEL
Date: 20211209

ACTIVE INGREDIENTS: NIACINAMIDE 2 g/100 mL; ADENOSINE 0.04 g/100 mL
INACTIVE INGREDIENTS: GLYCERIN; BUTYLENE GLYCOL; WATER

INCELLDERM VIETON OILMIST

ACTIVE INGREDIENTS

Niacinamide, Adenosine

INACTIVE INGREDIENTS

HippophaeRhamnoides Water, Caprylic/Capric Triglyceride, Butylene Glycol,1,2-Hexanediol, Glycerin, Hydroxyacetophenone, Propanediol, Water, Artemisia Capillaris Extract, Citrus Aurantium Bergamia (Bergamot) Fruit Oil, Betaine, Camellia Japonica Seed Oil, Rosa Canina Fruit Oil, Cereus Grandiflorus (Cactus) Extract, Hydrogenated Lecithin, Lavandula Angustifolia (Lavender) Oil, Sodium Chloride, Olea Europaea (Olive) Fruit Extract, Phytosteryl/OctyldodecylLauroyl Glutamate, Centella Asiatica Extract, Ceramide NP, Polygonum Cuspidatum Root Extract, ScutellariaBaicalensis Root Extract, Camellia Sinensis Leaf Extract, Glycyrrhiza Uralensis (Licorice) Root Extract, Rosmarinus Officinalis (Rosemary) Leaf Extract, Chamomilla Recutita (Matricaria) Flower Extract, Fucus Vesiculosus Extract, Prunella Vulgaris Extract, Thymus Vulgaris (Thyme) Flower/Leaf/Stem Extract, Lavandula Angustifolia (Lavender) Flower Extract, Origanum Vulgare Extract, Sodium Hyaluronate, Limonene, Linalool, Citral

PURPOSE

Helps to brighten the skin.

Helps to improve wrinkles in the skin.

WARNINGS

1. Consult a physician if red spots, swollenness, itchiness, or any other abnormal symptoms or side effects develops on the applied area during or after use or under direct sunlight.

2. Do not use on wound, etc.

3. Precautions for handling and storage

a) Keep out of the reach of children

b) Avoid direct sunlight

KEEP OUT OF REACH OF CHILDREN

Uses

Use at any time, lightly shaking up/down and spraying evenly, after adjusting the distance based on skin type. Wait until naturally absorbed

Directions

for external use only